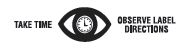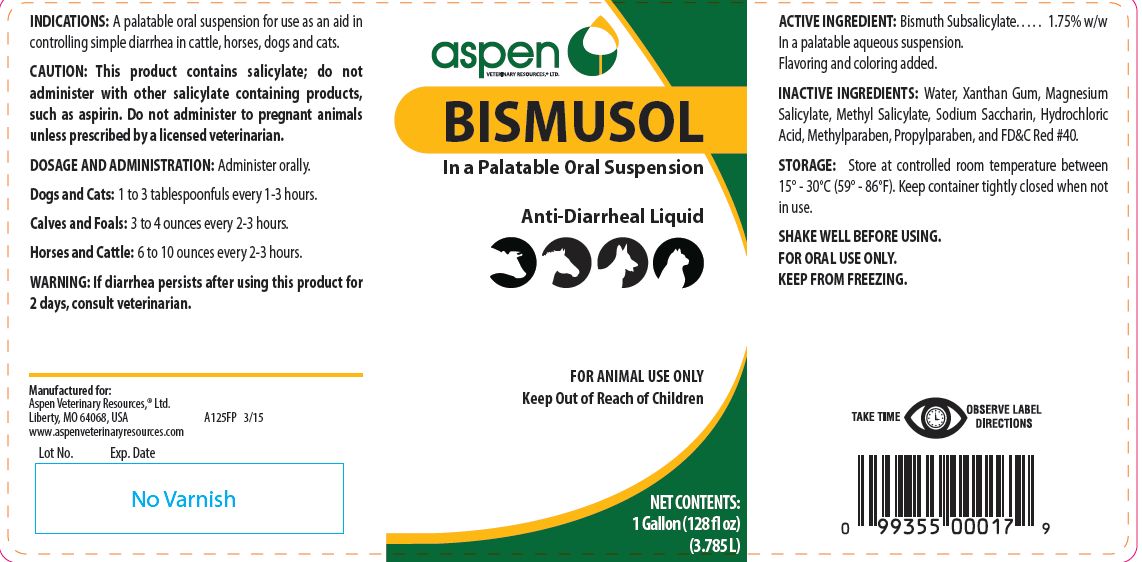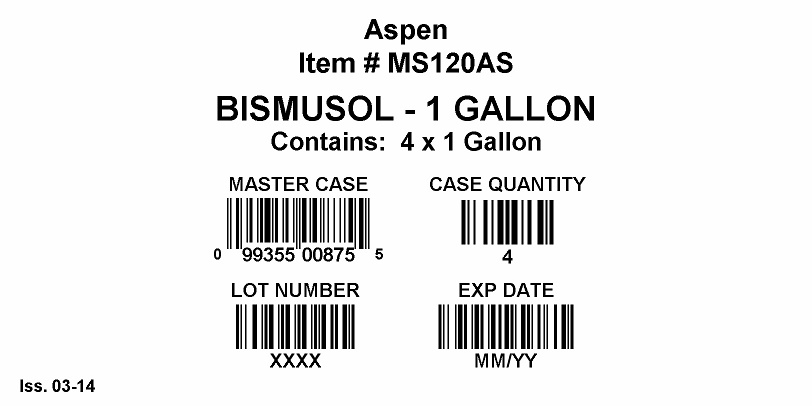 DRUG LABEL: BISMUSOL
NDC: 46066-221 | Form: SUSPENSION
Manufacturer: Aspen Veterinary
Category: animal | Type: OTC ANIMAL DRUG LABEL
Date: 20221114

ACTIVE INGREDIENTS: BISMUTH SUBSALICYLATE 17.4 g/1 L

BISMUSOL
In a Palatable Oral Suspension

PURPOSE

Anti-Diarrheal Liquid

KEEP OUT OF REACH OF CHILDREN

FOR ANIMAL USE ONLY
Keep Out of Reach of Children

INDICATIONS:

A palatable oral suspension for use as an aid in controlling simple diarrhea in cattle, horses, dogs and cats.

CAUTION:

This product contains salicylate; do not administer with other salicylate containing products, such as aspirin. Do not administer to pregnant animals unless prescribed by a licensed veterinarian.

DOSAGE AND ADMINISTRATION:

Administer orally.
Dogs and Cats: 1 to 3 tablespoonfuls every 1-3 hours.
Calves and Foals: 3 to 4 ounces every 2-3 hours.
Horses and Cattle: 6 to 10 ounces every 2-3 hours.

WARNING:

If diarrhea persists after using this product for 2 days, consult veterinarian.

ACTIVE INGREDIENT:

Bismuth Subsalicylate. . . . . 1.75% w/w
In a palatable aqueous suspension.
Flavoring and coloring added.

INACTIVE INGREDIENTS:

Water, Xanthan Gum, Magnesium Salicylate, Methyl Salicylate, Sodium Saccharin, Hydrochloric Acid, Methylparaben, Propylparaben, and FD&C Red #40.

STORAGE:

Store at controlled room temperature between 15° - 30°C (59° - 86°F). Keep container tightly closed when not in use.
SHAKE WELL BEFORE USING.
FOR ORAL USE ONLY.
KEEP FROM FREEZING.

NET CONTENTS:

1 Gallon (128 fl oz) (3.785 L)

INFORMATION FOR OWNERS/CAREGIVERS

Manufactured for:
Aspen Veterinary Resources,® Ltd.
Liberty, MO 64068, USA A125FP 3/15
www.aspenveterinaryresources.com

Bottle Label

Case Label